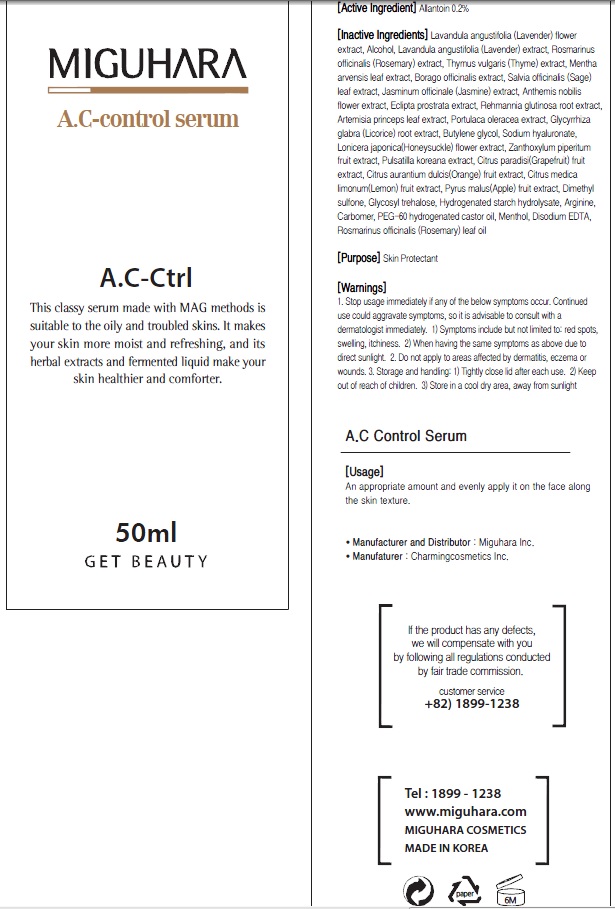 DRUG LABEL: AC Control Serum
NDC: 70380-070 | Form: CREAM
Manufacturer: MIGUHARA
Category: otc | Type: HUMAN OTC DRUG LABEL
Date: 20160218

ACTIVE INGREDIENTS: Allantoin 0.1 g/50 mL
INACTIVE INGREDIENTS: LAVANDULA ANGUSTIFOLIA FLOWER; Alcohol

ACTIVE INGREDIENT

Active Ingredient: Allantoin 0.2%

INACTIVE INGREDIENT

Inactive Ingredients: Lavandula angustifolia (Lavender) flower extract, Alcohol, Lavandula angustifolia (Lavender) extract, Rosmarinus officinalis (Rosemary) extract, Thymus vulgaris (Thyme) extract, Mentha arvensis leaf extract, Borago officinalis extract, Salvia officinalis (Sage) leaf extract, Jasminum officinale (Jasmine) extract, Anthemis nobilis flower extract, Eclipta prostrata extract, Rehmannia glutinosa root extract, Artemisia princeps leaf extract, Portulaca oleracea extract, Glycyrrhiza glabra (Licorice) root extract, Butylene glycol, Sodium hyaluronate, Lonicera japonica(Honeysuckle) flower extract, Zanthoxylum piperitum fruit extract, Pulsatilla koreana extract, Citrus paradisi(Grapefruit) fruit extract, Citrus aurantium dulcis(Orange) fruit extract, Citrus medica limonum(Lemon) fruit extract, Pyrus malus(Apple) fruit extract, Dimethyl sulfone, Glycosyl trehalose, Hydrogenated starch hydrolysate, Arginine, Carbomer, PEG-60 hydrogenated castor oil, Menthol, Disodium EDTA, Rosmarinus officinalis (Rosemary) leaf oil

PURPOSE

Purpose: Skin Protectant

WARNINGS

1. Stop usage immediately if any of the below symptoms occur. Continued use could aggravate symptoms, so it is advisable to consult with a dermatologist immediately. 1) Symptoms include but not limited to: red spots, swelling, itchiness. 2) When having the same symptoms as above due to direct sunlight. 2. Do not apply to areas affected by dermatitis, eczema or wounds. 3. Storage and handling: 1) Tightly close lid after each use. 2 Keep out of reach of children 3) Store in a cool dry area, away from sunlight

KEEP OUT OF REACH OF CHILDREN

Usage

Usage: An appropriate amount and evenly apply it on the face along the skin texture.

Usage

Usage: An appropriate amount and evenly apply it on the face along the skin texture.